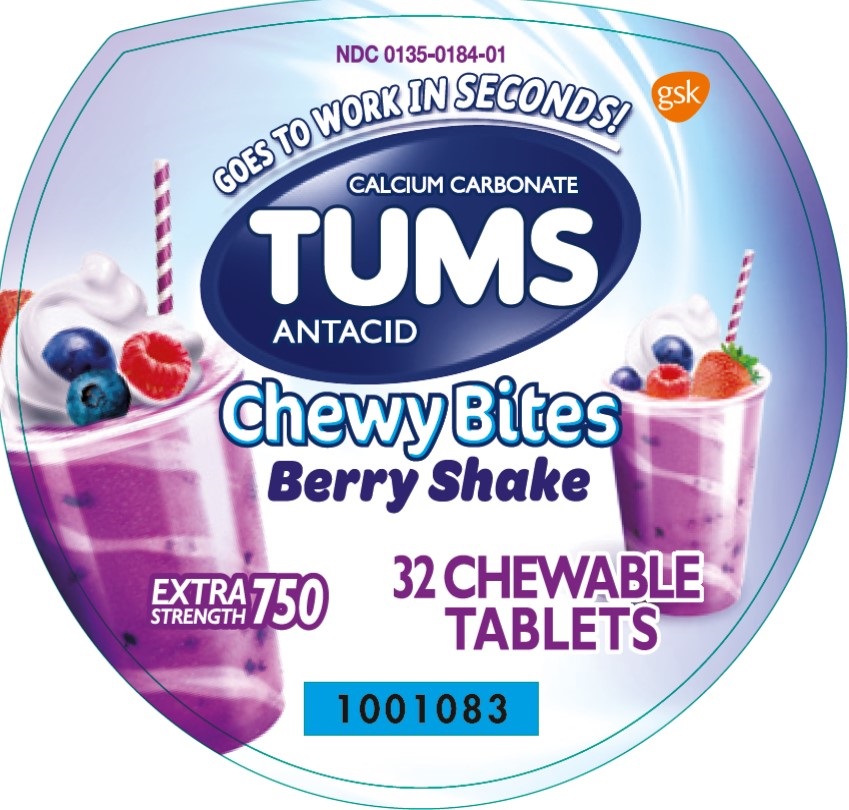 DRUG LABEL: Tums Chewy Bites

NDC: 0135-0184 | Form: TABLET, CHEWABLE
Manufacturer: Haleon US Holdings LLC
Category: otc | Type: HUMAN OTC DRUG LABEL
Date: 20240302

ACTIVE INGREDIENTS: CALCIUM CARBONATE 750 mg/1 1
INACTIVE INGREDIENTS: ACACIA; ALCOHOL; AMMONIA; YELLOW WAX; CARMINIC ACID; CARNAUBA WAX; CITRIC ACID MONOHYDRATE; COCONUT OIL; STARCH, CORN; CORN SYRUP; ICODEXTRIN; ETHYL ACETATE; FD&C BLUE NO. 1; ALUMINUM OXIDE; FD&C BLUE NO. 2; FD&C RED NO. 40; FD&C YELLOW NO. 6; ISOPROPYL ALCOHOL; MALTODEXTRIN; METHYLPARABEN; BUTYL ALCOHOL; PHOSPHORIC ACID; PROPYLENE GLYCOL; PROPYLPARABEN; WATER; SHELLAC; SORBIC ACID; SORBITOL; SOYBEAN OIL; LECITHIN, SOYBEAN; SUCROSE; TERT-BUTYLHYDROQUINONE; TITANIUM DIOXIDE; CORN OIL

Drug Facts

Active ingredient (per tablet)

Calcium carbonate 750 mg

Purpose

Antacid

Uses

relieves

- heartburn
- acid indigestion
- sour stomach
- upset stomach associated with these symptoms

Warnings

Ask a doctor or pharmacist before use if you are

presently taking a prescription drug. Antacids may interact with certain prescription drugs.

When using this product

- do not take more than 6 tablets in 24 hours
- if pregnant do not take more than 6 tablets in 24 hours
- do not use the maximum dosage for more than 2 weeks, except under the advice and supervision of a doctor

Directions

- adults and children 12 years of age and over:chew 2-4 tablets as symptoms occur, or as directed by a doctor. Chew or crush tablets completely before swallowing.
- do not take for symptoms that persist for more than 2 weeks, unless advised by a doctor

Other Information

- each chewable tablet contains:elemental calcium 305 mg
- do not store above 25°C (77°F)

Inactive ingredients

Acacia gum, alcohol, ammonium hydroxide, beeswax, carmine, carnauba wax, citric acid, coconut oil, corn starch, corn syrup, dextrin, ethyl acetate, ethyl alcohol, FD&C blue no. 1 aluminum lake, FD&C blue no. 2 aluminum lake, FD&C red no. 40 aluminum lake, FD&C yellow no. 6 aluminum lake, flavors, gum arabic, isopropyl alcohol, maltodextrin, methyl paraben, n-butyl alcohol, phosphoric acid, propylene glycol, propylparaben, purified water, shellac, sorbic acid, sorbitol, soybean oil, soy lecithin, sucrose, tertiary butylhydroquinone, titanium dioxide, vegetable oil

Questions or comments?

Call 1-800-897-7535

Principal Display Panel

NDC 0135-0184-01

TUMS

CALCIUM CARBONATE

ANTACID

Chewy Bites

Berry Shake

GOES TO WORK IN SECONDS!

EXTRA STRENGTH 750

32 CHEWABLE TABLETS

Safety sealed –

Do not use if printed inner seal beneath cap is missing or broken.

Distributed by:

GSK Consumer Healthcare

Warren, NJ 07059

Trademarks are owned by or licensed to the GSK group of companies.

©2020 GSK or licensor.

Front Label: 1001083

Back Label: 1001084